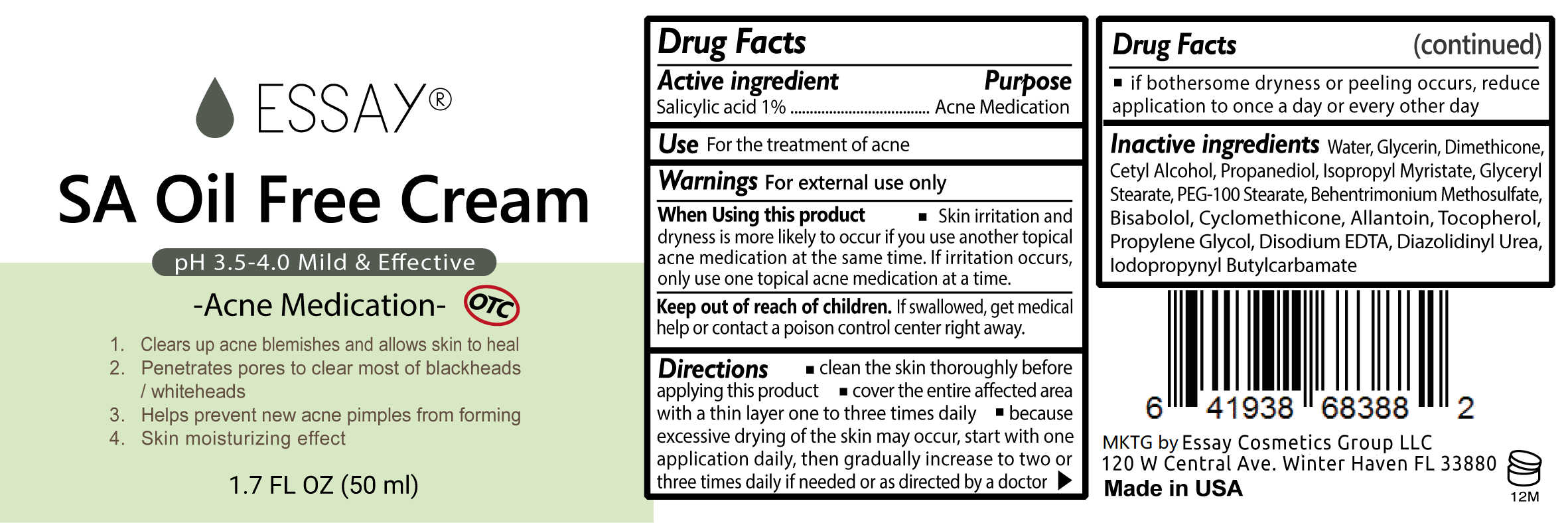 DRUG LABEL: SA Oil Free Cream
NDC: 72900-882 | Form: CREAM
Manufacturer: Essay Cosmetics Group LLC
Category: otc | Type: HUMAN OTC DRUG LABEL
Date: 20190417

ACTIVE INGREDIENTS: SALICYLIC ACID 0.5 g/0.5 g
INACTIVE INGREDIENTS: DIAZOLIDINYL UREA; DIMETHICONE 350; IODOPROPYNYL BUTYLCARBAMATE; PEG-100 STEARATE; BEHENTRIMONIUM METHOSULFATE; CYCLOMETHICONE; ALLANTOIN; .ALPHA.-TOCOPHEROL, D-; 1,2-PROPANEDIOL, 1-BENZOATE; .ALPHA.-BISABOLOL, (+/-)-; GLYCERIN; GLYCERYL MONOSTEARATE; WATER; CETYL ALCOHOL; PROPANEDIOL; ISOPROPYL MYRISTATE; MAGNESIUM DISODIUM EDTA

SA Oil Free Cream-Essay

Active Ingredient

Acne medication, 1% Salicylic Acid

PURPOSE

Acne Medication

Use

Use ■ for treatmant of acne

WARNINGS

Warnings ■ for external use only ■ skin irritation and dryness is more likely to occur if you use another topical acne medication at the same time ■ if irritation occurs, only use one topical acne medication at a time

INSTRUCTIONS FOR USE

Directions ■ clean the skin thoroughly before applying this product ■ cover the entire affected area with a thin layer one to three times daily ■ because excessive drying of the skin may occur, start with one application daily, then gradually increase to two or three times daily if needed or as directed by a doctor ■ if bothersome dryness or peeling occurs, reduce application to once a day or every other day.

INACTIVE INGREDIENT

Inactive ingredients Water, Glycerin, Dimethicone, Cetyl Alcohol, Propanediol, Isopropyl Myristate, Glyceryl Stearate, PEG-100 Stearate, Behentrimonium Methosulfate, Bisabolol, Cyclomethicone, Allantoin, Butylene Glycol, Tocopheryl Acetate, Propylene Glycol, Disodium EDTA, Diazolidinyl Urea, Iodopropynyl Butylcarbamate

KEEP OUT OF REACH OF CHILDREN

If swallowed, get medical help or contact a Poison Control Center immediately.

DOSAGE AND ADMINISTRATION

● clean the skin thoroughly before applying this product
● cover the entire affected area with a thin layer one to three times daily
● because excessive drying of the skin may occur, start with one application daily, then gradually increase to two or three times daily if needed or as directed by a doctor
● if bothersome dryness or peeling occurs, reduce application to once a day or every other day.